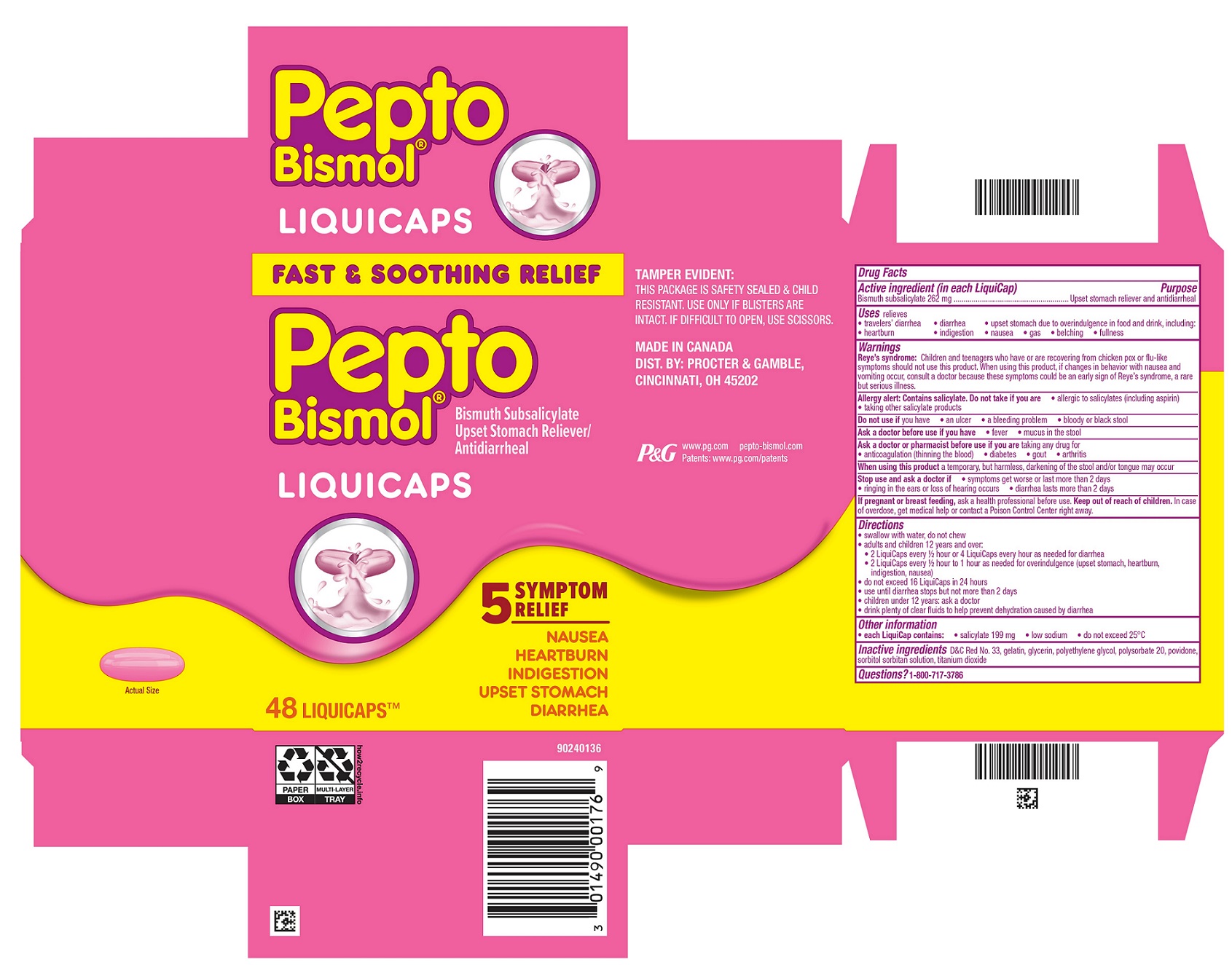 DRUG LABEL: Pepto Bismol
NDC: 37000-535 | Form: CAPSULE, LIQUID FILLED
Manufacturer: The Procter & Gamble Manufacturing Company
Category: otc | Type: HUMAN OTC DRUG LABEL
Date: 20251001

ACTIVE INGREDIENTS: BISMUTH SUBSALICYLATE 262 mg/1 1
INACTIVE INGREDIENTS: POLYSORBATE 20; SORBITOL; TITANIUM DIOXIDE; GELATIN; POVIDONE; D&C RED NO. 33; POLYETHYLENE GLYCOL 400; GLYCERIN

Pepto Bismol® LiquiCaps

Drug Facts

Active ingredient (in each LiquiCap)

Bismuth subsalicylate 262 mg

Purpose

Upset stomach reliever and antidiarrheal

Uses

relieves

- travelers' diarrhea
- diarrhea
- upset stomach due to overindulgence in food and drink, including:
- heartburn
- indigestion
- nausea
- gas
- belching
- fullness

Warnings

Reye's syndrome:

Children and teenagers who have or are recovering from chicken pox or flu-like symptoms should not use this product. When using this product, if changes in behavior with nausea and vomiting occur, consult a doctor because these symptoms could be an early sign of Reye's syndrome, a rare but serious illness.

Allergy alert:

Contains salicylate. Do not take if you are

- allergic to salicylates (including aspirin)
- taking other salicylate products

Do not use if

you have

- an ulcer
- a bleeding problem
- bloody or black stool

Ask a doctor before use if you have

- fever
- mucus in the stool

Ask a doctor or pharmacist before use if you are

taking any drug for

- anticoagulation (thinning the blood)
- diabetes
- gout
- arthritis

When using this product

a temporary, but harmless, darkening of the stool and/or tongue may occur

Stop use and ask a doctor if

- symptoms get worse or last more than 2 days
- ringing in the ears or loss of hearing occurs
- diarrhea lasts more than 2 days

If pregnant or breast feeding,

ask a health professional before use.

Keep out of reach of children.

OVERDOSAGE

In case of overdose, get medical help or contact a Poison Control Center right away.

Directions

• swallow with water, do not chew
• adults and children 12 years and over:
• 2 LiquiCaps every ½ hour or 4 LiquiCaps every hour as needed for diarrhea
• 2 LiquiCaps every ½ hour to 1 hour as needed for overindulgence (upset stomach, heartburn, indigestion, nausea)
• do not exceed 16 LiquiCaps in 24 hours
• use until diarrhea stops but not more than 2 days
• children under 12 years: ask a doctor
• drink plenty of clear fluids to help prevent dehydration caused by diarrhea

Other information

• each LiquiCap contains:

• salicylate 199 mg

• low sodium

• do not exceed 25°C

Inactive ingredients

D&C Red No. 33, gelatin, glycerin, polyethylene glycol, polysorbate 20, povidone, sorbitol sorbitan solution, titanium dioxide

Questions?

1-800-717-3786

TAMPER EVIDENT: THIS PACKAGE IS SAFETY SEALED & CHILD RESISTANT. USE ONLY IF BLISTERS ARE INTACT. IF DIFFICULT TO OPEN, USE SCISSORS.

MADE IN CANADA
DIST. BY PROCTER & GAMBLE,

CINCINNATI OH 45202

PRINCIPAL DISPLAY PANEL - 48 LiquiCap Carton

FAST & SOOTHING RELIEF

Pepto
Bismol®

Bismuth Subsalicylate

Upset Stomach Reliever/Antidiarrheal

LIQUICAPS

5 SYMPTOM RELIEF

NAUSEA

HEARTBURN

INDIGESTION

UPSET STOMACH

DIARRHEA

48 LIQUICAPS™